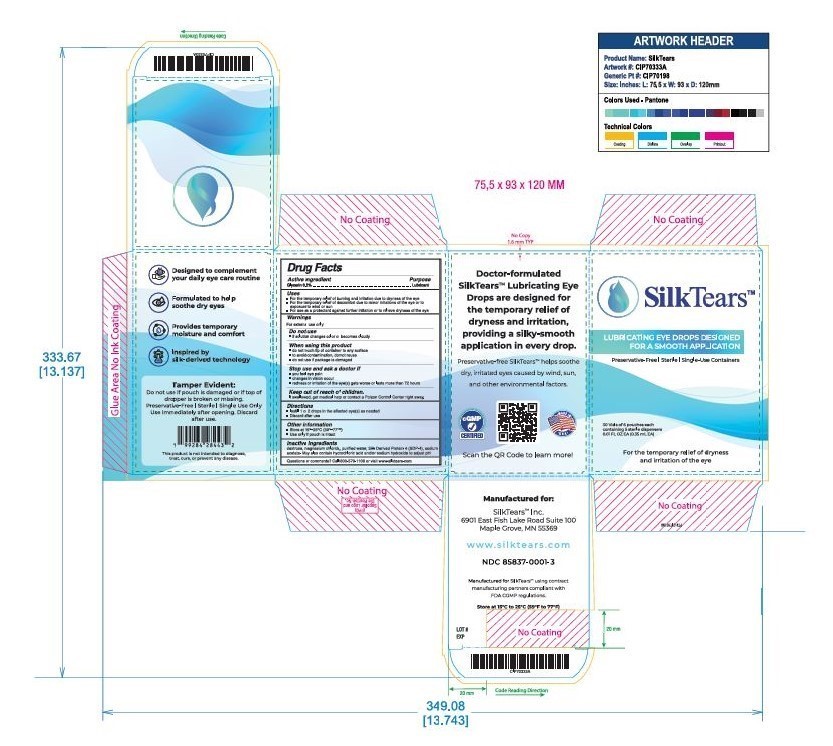 DRUG LABEL: SilkTears
NDC: 85837-0001 | Form: SOLUTION/ DROPS
Manufacturer: SilkTears
Category: otc | Type: HUMAN OTC DRUG LABEL
Date: 20250716

ACTIVE INGREDIENTS: GLYCERIN 2 mg/1000 mL
INACTIVE INGREDIENTS: DEXTROSE; MAGNESIUM CHLORIDE; AMLISIMOD 10 mg/1000 mL; SODIUM ACETATE; WATER; HYDROCHLORIC ACID; SODIUM HYDROXIDE

Purpose

Lubricant

Dosage and Administration

Instill 1 to 2 drops in the affected eye(s) as needed.

WARNINGS

For external use only.

Do not use if solution changes color or becomes cloudy.

When using this product:
- do not touch tip of container to any surface to avoid contamination
- do not reuse
- once opened, discard

Stop use and ask a doctor if you experience:
- eye pain
- changes in vision
- continued redness or irritation

Keep out of reach of children. If swallowed, get medical help or contact a Poison Control Center right away.

INACTIVE INGREDIENT

Inactive ingredients: dextrose, magnesium chloride, purified water, Silk-Derived Protein-4 (SDP-4), sodium acetate. May also contain hydrochloric acid and/or sodium hydroxide to adjust PH

INDICATIONS AND USAGE

For the temporary relief of burning and irritation due to dryness of the eye.

Keep out of reach of children. If swallowed, get medical help or contact a Poison Control Center right away.

ACTIVE INGREDIENT

Glycerin 0.2% – Lubricant

PACKAGE LABEL

30 vials of 6 pouches each containing 5 sterile dispensers 0.01 FL OZ (0.35 mL EA)